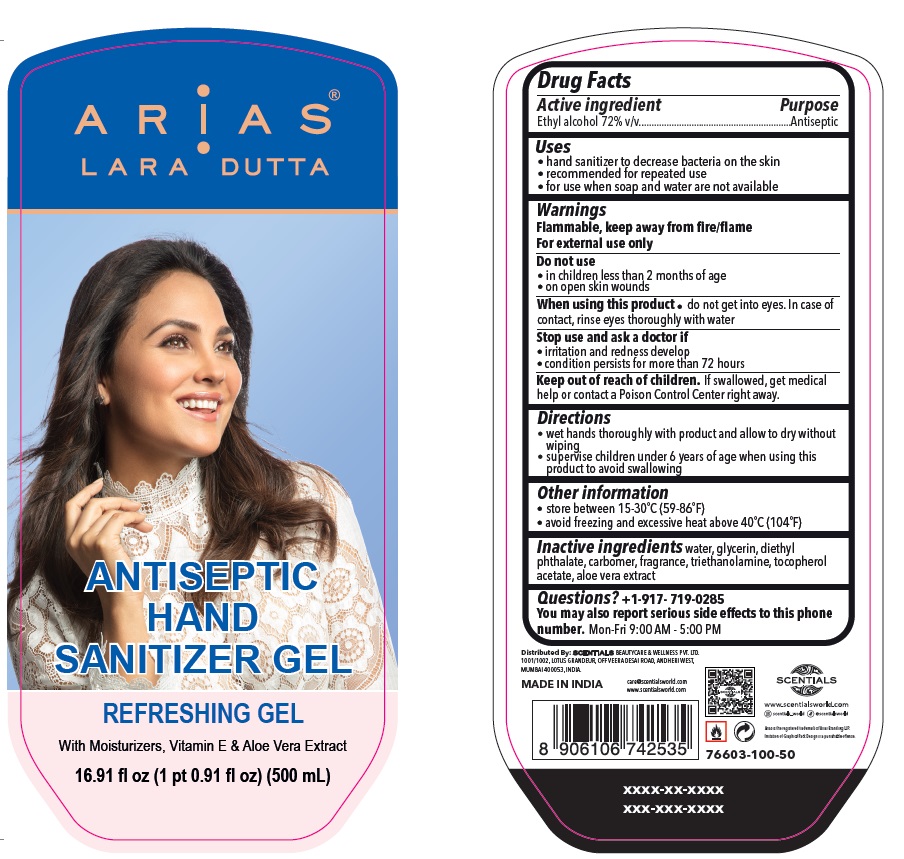 DRUG LABEL: ARiAS ANTISEPTIC HAND SANITIZER
NDC: 76603-100 | Form: GEL
Manufacturer: Scentials Beautycare And Wellness Private Limited
Category: otc | Type: HUMAN OTC DRUG LABEL
Date: 20200711

ACTIVE INGREDIENTS: ALCOHOL 72 mL/100 mL
INACTIVE INGREDIENTS: WATER; GLYCERIN; DIETHYL PHTHALATE; CARBOMER HOMOPOLYMER, UNSPECIFIED TYPE; TROLAMINE; .ALPHA.-TOCOPHEROL ACETATE; ALOE VERA LEAF

ARiAS® ANTISEPTIC HAND SANITIZER GEL

Active ingredient

Ethyl alcohol 72% v/v

Purpose

Antiseptic

Uses

• hand sanitizer to decrease bacteria on the skin

• recommended for repeated use

• for use when soap and water are not available

Warnings

Flammable, keep away from fire/flame

For external use only

Do not use

• in children less than 2 months of age

• on open skin wounds

When using this product • do not get into eyes. In case of contact, rinse eyes thoroughly with water

Stop use and ask a doctor if

• irritation and redness develop

• condition persists for more than 72 hours

Keep out of reach of children. If swallowed, get medical help or contact a Poison Control Center right away.

Directions

• wet hands thoroughly with product and allow to dry without wiping

• supervise children under 6 years of age when using this product to avoid swallowing

Other information

• store between 15-30°C (59-86°F)

• avoid freezing and excessive heat above 40°C (104°F)

Inactive ingredients

water, glycerin, diethylphthalate, carbomer, fragrance, triethanolamine, tocopherol acetate, aloe vera extract

Questions?

+1-917- 719-0285

You may also report serious side effects to this phone number. Mon-Fri 9:00 AM - 5:00 PM

LARA DUTTA

REFRESHING GEL

With Moisturizers, Vitamin E & Aloe Vera Extract

Distributed By: SCENTIALS BEAUTYCARE & WELLNESS PVT. LTD.

1001/1002, LOTUS GRANDEUR, OFF VEERA DESAI ROAD, ANDHERI WEST,

MUMBAI 400053, INDIA.

MADE IN INDIA

care@scentialsworld.com

www.scentialsworld.com

scentials_world @scentialsworld

Arias is the registered trademark of Arias Branding LLP.

Imitation of Graphics/Pack Design is a punishable offence.